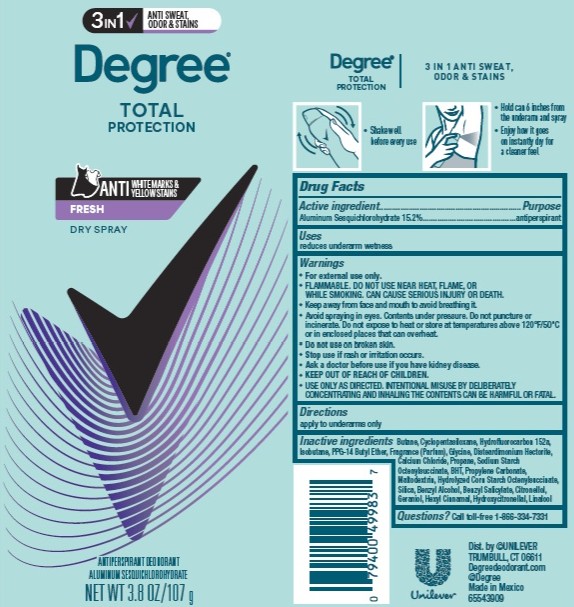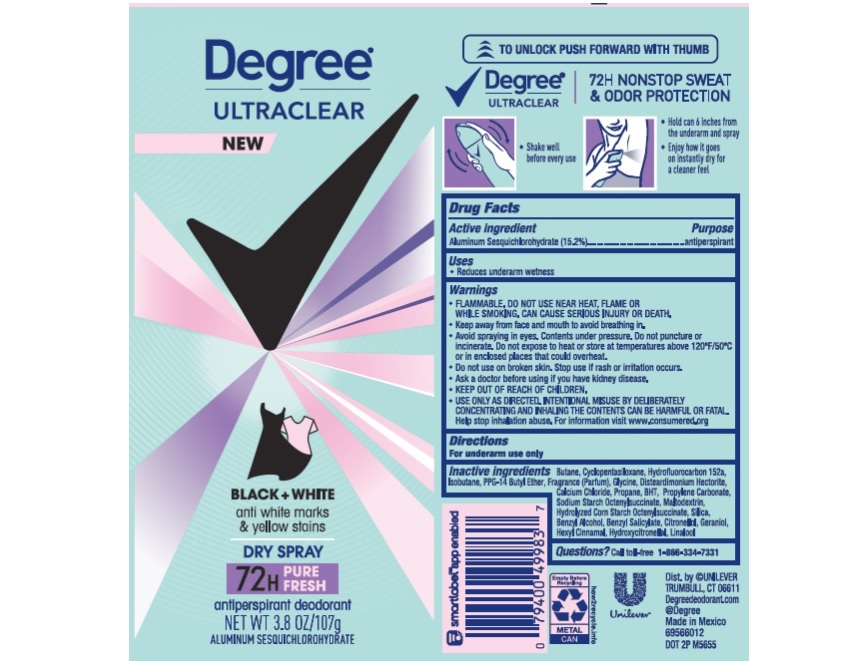 DRUG LABEL: Degree
NDC: 64942-2047 | Form: AEROSOL, SPRAY
Manufacturer: Conopco, Inc. d/b/a Unilever
Category: otc | Type: HUMAN OTC DRUG LABEL
Date: 20260212

ACTIVE INGREDIENTS: ALUMINUM SESQUICHLOROHYDRATE 15.2 g/100 g
INACTIVE INGREDIENTS: .BETA.-CITRONELLOL, (R)-; PPG-14 BUTYL ETHER; BUTANE; 1,1-DIFLUOROETHANE; CYCLOMETHICONE 5; ISOBUTANE; DISTEARDIMONIUM HECTORITE; CALCIUM CHLORIDE; PROPANE; BUTYLATED HYDROXYTOLUENE; PROPYLENE CARBONATE; MALTODEXTRIN; SILICON DIOXIDE; GLYCINE; .ALPHA.-HEXYLCINNAMALDEHYDE; LINALOOL, (+/-)-; BENZYL ALCOHOL; BENZYL SALICYLATE; GERANIOL; HYDROXYCITRONELLAL

Degree Advanced Ultraclear Black + White Pure Fresh Dry Spray 72H Antiperspirant Deodorant

Drug Facts

Active ingredient

Aluminum Sesquichlorohydrate (15.2%)

Purpose

antiperspirant

Uses

reduces underarm wetness

Warnings

• FLAMMABLE. DO NOT USE NEAR HEAT, FLAME, OR WHILE SMOKING. CAN CAUSE SERIOUS INJURY OR DEATH
• Keep away from face and mouth to avoid breathing in.
• Avoid spraying in eyes. Contents under pressure. Do not puncture or incinerate. Do not expose to heat or store at temperatures above 120°F/50°C or in enclosed places that could overheat
• Do not use on broken skin. Stop use if rash or irritation occurs.
• Ask a doctor before using if you have kidney disease.
• USE ONLY AS DIRECTED. INTENTIONAL MISUSE BY DELIBERATELY CONCENTRATING AND INHALING THE CONTENTS CAN BE HARMFUL OR FATAL.
Help stop inhalation abuse. For information visit www.inhalant.org

• KEEP OUT OF REACH OF CHILDREN

Directions

For underarms use only

Inactive ingredients

Butane, Cyclopentasiloxane, Hydrofluorocarbon 152a, Isobutane, PPG-14 Butyl Ether, Fragrance (Parfum), Glycine, Disteardimonium Hectorite, Calcium Chloride, Propane, BHT, Propylene Carbonate, Sodium Starch Octenylsuccinate, Maltodextrin, Hydrolyzed Corn Starch Octenylsuccinate, Silica. Benzyl Alcohol, Benzyl Salicylate, Citronellol, Geraniol, Hexyl Cinnamal, Hydroxycitronellal, Linalool

Questions?

Call toll-free 1-866-334-7331